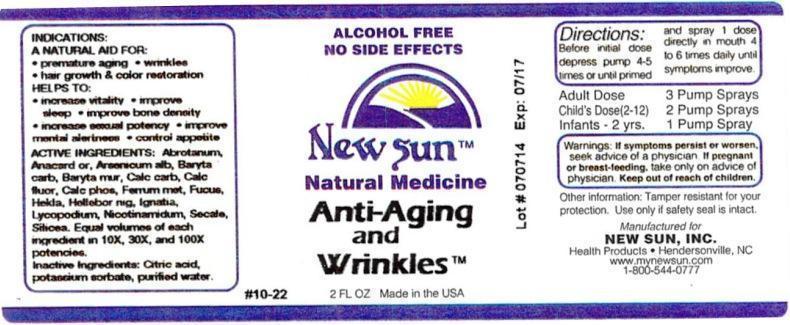 DRUG LABEL: Anti-Aging and Wrinkles
NDC: 66579-0069 | Form: LIQUID
Manufacturer: New Sun Inc.
Category: homeopathic | Type: HUMAN OTC DRUG LABEL
Date: 20140729

ACTIVE INGREDIENTS: ARTEMISIA ABROTANUM FLOWERING TOP 10 [hp_X]/59 mL; SEMECARPUS ANACARDIUM JUICE 10 [hp_X]/59 mL; ARSENIC TRIOXIDE 10 [hp_X]/59 mL; BARIUM CARBONATE 10 [hp_X]/59 mL; BARIUM CHLORIDE DIHYDRATE 10 [hp_X]/59 mL; OYSTER SHELL CALCIUM CARBONATE, CRUDE 10 [hp_X]/59 mL; CALCIUM FLUORIDE 10 [hp_X]/59 mL; TRIBASIC CALCIUM PHOSPHATE 10 [hp_X]/59 mL; IRON 10 [hp_X]/59 mL; FUCUS VESICULOSUS 10 [hp_X]/59 mL; HEKLA LAVA 10 [hp_X]/59 mL; HELLEBORUS NIGER ROOT 10 [hp_X]/59 mL; STRYCHNOS IGNATII SEED 10 [hp_X]/59 mL; LYCOPODIUM CLAVATUM SPORE 10 [hp_X]/59 mL; NIACINAMIDE 10 [hp_X]/59 mL; CLAVICEPS PURPUREA SCLEROTIUM 10 [hp_X]/59 mL; SILICON DIOXIDE 10 [hp_X]/59 mL
INACTIVE INGREDIENTS: CITRIC ACID MONOHYDRATE; POTASSIUM SORBATE; WATER

Anti-Aging and Wrinkles

DOSAGE AND ADMINISTRATION

Directions: Before initial dose depress pump 4-5 times or until primed and spray 1 dose directly in mouth 4 to 6 times daily until symptoms improve.

Adult Dose: 3 Pump Sprays

Child's Dose (2-12): 2 Pump Sprays

Infants - 2 yrs: 1 Pump Spray

WARNINGS

Warnings: If symptoms persist or worsen, seek advice of physician. If pregnant or breast-feeding, take only on advice of physician.

Keep out of reach of children.

Other information: Tamper resistant for your protection. Use only if safety seal is intact.

PURPOSE

Indications: A natural aid for: •premature aging •wrinkles •hair growth & color restoration

Helps to: •increase vitality •improve sleep •improve bone density •increase sexual potency •improve mental alertness •control appetite

ACTIVE INGREDIENT

Active Ingredients: Abrotanum, Anacardium orientale, Arsenicum album, Baryta carbonica, Baryta muriatica, Calcarea carbonica, Calcarea fluorica, Calcarea phosphorica, Ferrum metallicum, Fucus vesiculosus, Hekla lava, Helleborus niger, Ignatia amara, Lycopodium clavatum, Nicotinamidum, Secale cornutum, Silicea. Equal volumes of each ingredient in 10X, 30X, and 100X potencies.

Inactive Ingredient: Citric acid, potassium sorbate, purified water.

Indications: A NATURAL AID FOR:

- premature aging
- wrinkles
- hair growth & color restoration

HELPS TO:

- increase vitality
- improve sleep
- improve bone density
- increase sexual potency
- improve mental alertness
- control appetite